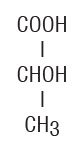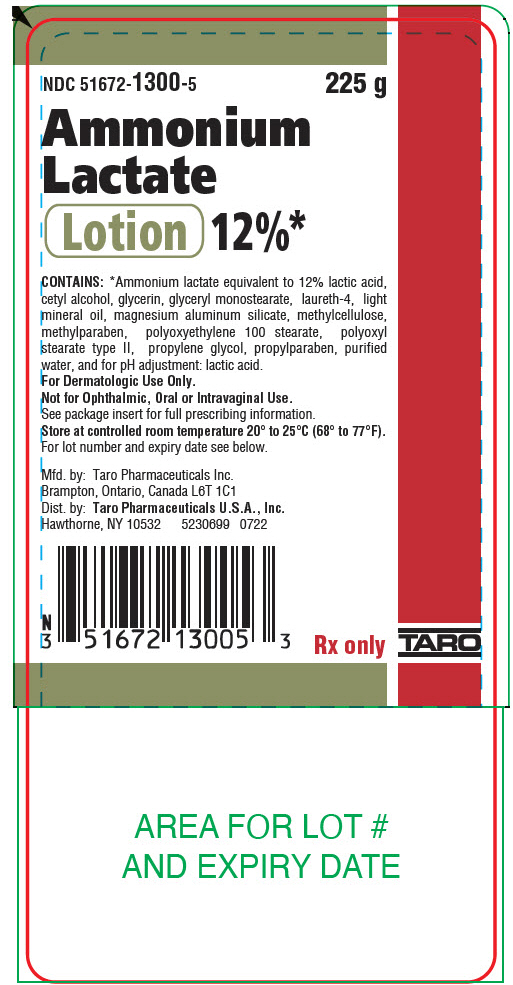 DRUG LABEL: Ammonium Lactate
NDC: 51672-1300 | Form: LOTION
Manufacturer: Sun Pharmaceutical Industries, Inc.
Category: prescription | Type: HUMAN PRESCRIPTION DRUG LABEL
Date: 20250701

ACTIVE INGREDIENTS: AMMONIUM LACTATE 120 mg/1 g
INACTIVE INGREDIENTS: GLYCERYL MONOSTEARATE; PEG-100 STEARATE; POLYOXYL 40 STEARATE; LAURETH-4; CETYL ALCOHOL; LIGHT MINERAL OIL; METHYLPARABEN; PROPYLPARABEN; WATER; MAGNESIUM ALUMINUM SILICATE; PROPYLENE GLYCOL; GLYCERIN

Ammonium
Lactate
Lotion 12%*

Rx only

For Dermatologic Use Only.
Not for Ophthalmic, Oral or Intravaginal Use.

DESCRIPTION

*Ammonium Lactate Lotion, 12% specially formulates 12% lactic acid, as ammonium lactate to provide a lotion pH of 4.5 to 5.5. Ammonium Lactate Lotion also contains cetyl alcohol, glycerin, glyceryl monostearate, laureth-4, light mineral oil, magnesium aluminum silicate, methylcellulose, methylparaben, polyoxyethylene 100 stearate, polyoxyl stearate type II, propylene glycol, propylparaben, purified water, and for pH adjustment: lactic acid. Lactic acid is a racemic mixture of 2-hydroxypropanoic acid and has the following structural formula:

CLINICAL PHARMACOLOGY

Lactic acid is an alpha-hydroxy acid. It is a normal constituent of tissues and blood. The alpha-hydroxy acids (and their salts) may act as humectants when applied to the skin. This property may influence hydration of the stratum corneum. In addition, lactic acid, when applied to the skin, may act to decrease corneocyte cohesion. The mechanism(s) by which this is accomplished is not yet known. An in vitrostudy of percutaneous absorption of Ammonium Lactate Lotion using human cadaver skin indicates that approximately 5.8% of the material was absorbed after 68 hours.

INDICATIONS AND USAGE

Ammonium Lactate Lotion is indicated for the treatment of dry, scaly skin (xerosis) and ichthyosis vulgaris and for temporary relief of itching associated with these conditions.

CONTRAINDICATIONS

Ammonium Lactate Lotion is contraindicated in those patients with a history of hypersensitivity to any of the label ingredients.

WARNINGS

Sun exposure to areas of the skin treated with Ammonium Lactate Lotion, 12% should be minimized or avoided (see PRECAUTIONSsection). The use of Ammonium Lactate Lotion should be discontinued if hypersensitivity is observed.

PRECAUTIONS

General

For external use only. Stinging or burning may occur when applied to skin with fissures, erosions or that is otherwise abraded (for example, after shaving the legs). Caution is advised when used on the face because of the potential for irritation. The potential for post-inflammatory hypo- or hyperpigmentation has not been studied.

Information for Patients

Patients using Ammonium Lactate Lotion, 12% should receive the following information and instructions:

1. This medication is to be used as directed by the physician, and should not be used for any disorder other than for which it was prescribed. It is for external use only. Avoid contact with eyes, lips, or mucous membranes.
2. Patients should minimize or avoid use of this product on areas of the skin that may be exposed to natural or artificial sunlight, including the face. If sun exposure is unavoidable, clothing should be worn to protect the skin.
3. This medication may cause transient stinging or burning when applied to skin with fissures, erosions, or abrasions (for example, after shaving the legs).
4. If the skin condition worsens with treatment, the medication should be promptly discontinued.

Carcinogenesis, Mutagenesis, Impairment of Fertility

The topical treatment of CD-1 mice with 12%, 21% or 30% ammonium lactate formulations for two years did not produce a significant increase in dermal or systemic tumors in the absence of increased exposure to ultraviolet radiation. The maximum systemic exposure of the mice in this study was 0.7 times the maximum possible systemic exposure in humans. However, a long-term photocarcinogenicity study in hairless albino mice suggested that topically applied 12% ammonium lactate formulations enhanced the rate of ultraviolet light-induced skin tumor formation. The mutagenic potential of ammonium lactate formulations was evaluated in the Ames assay and in the mouse in vivomicronucleus assay, both of which were negative. In dermal Segment I and III studies with ammonium lactate formulations there were no effects observed in fertility or pre- or post-natal development parameters in rats at dose levels of 300 mg/kg/day (1800 mg/m^2/day), approximately 0.4 times the human topical dose.

Pregnancy

Teratogenic effects

Animal reproduction studies have been performed in rats and rabbits at doses up to 0.7 and 1.5 times the human dose respectively (600 mg/kg/day, corresponding to 3600 mg/m^2/day in the rat and 7200 mg/m^2/day in the rabbit) and have revealed no evidence of impaired fertility or harm to the fetus due to ammonium lactate formulations. There are, however, no adequate and well-controlled studies in pregnant women. Because animal reproduction studies are not always predictive of human response, Ammonium Lactate Lotion should be used during pregnancy only if clearly needed.

Nursing Mothers

Although lactic acid is a normal constituent of blood and tissues, it is not known to what extent this drug affects normal lactic acid levels in human milk. Because many drugs are excreted in human milk, caution should be exercised when Ammonium Lactate Lotion is administered to a nursing woman.

Pediatric Use

Safety and effectiveness of Ammonium Lactate Lotion have been demonstrated in infants and children. No unusual toxic effects were reported.

Geriatric Use

Clinical studies of Ammonium Lactate Lotion 12% did not include sufficient numbers of subjects aged 65 and over to determine whether they respond differently from younger subjects. Other reported clinical experience has not identified differences in responses between elderly and younger patients. In general, dose selection for an elderly patient should be cautious.

ADVERSE REACTIONS

The most frequent adverse experiences in patients with xerosis are transient stinging (1 in 30 patients), burning (1 in 30 patients), erythema (1 in 50 patients) and peeling (1 in 60 patients). Other adverse reactions which occur less frequently are irritation, eczema, petechiae, dryness and hyperpigmentation. Due to the more severe initial skin conditions associated with ichthyosis, there was a higher incidence of transient stinging, burning and erythema (each occurring in 1 in 10 patients).

OVERDOSAGE

The oral administration of Ammonium Lactate Lotion to rats and mice showed this drug to be practically non-toxic (LD50>15 mL/kg).

DOSAGE AND ADMINISTRATION

Shake well. Apply to the affected areas and rub in thoroughly. Use twice daily or as directed by a physician.

HOW SUPPLIED

225 g (NDC 51672-1300-5) plastic bottle and 400 g (NDC 51672-1300-9) plastic bottle.

STORAGE AND HANDLING

Store between 20° to 25°C (68° to 77°F)[see USP Controlled Room Temperature].

Mfd. by:
Taro Pharmaceuticals Inc.
Brampton, Ontario,
Canada L6T 1C1

Dist. by:
Taro Pharmaceuticals
U.S.A., Inc.
Hawthorne, NY 10532
Revised: July 2022

PRINCIPAL DISPLAY PANEL - 225 g Bottle Label

NDC 51672-1300-5

225 g

Ammonium
Lactate
Lotion 12%*

CONTAINS: *Ammonium lactate equivalent to 12% lactic acid,
cetyl alcohol, glycerin, glyceryl monostearate, laureth-4, light
mineral oil, magnesium aluminum silicate, methylcellulose,
methylparaben, polyoxyethylene 100 stearate, polyoxyl
stearate type II, propylene glycol, propylparaben, purified
water, and for pH adjustment: lactic acid.
For Dermatologic Use Only.
Not for Ophthalmic, Oral or Intravaginal Use.
See package insert for full prescribing information.
Store at controlled room temperature 20° to 25°C (68° to 77°F).
For lot number and expiry date see below.

Mfd. by: Taro Pharmaceuticals Inc.
Brampton, Ontario, Canada L6T 1C1
Dist. by: Taro Pharmaceuticals U.S.A., Inc.
Hawthorne, NY 10532
5230699
0722

Rx only

TARO